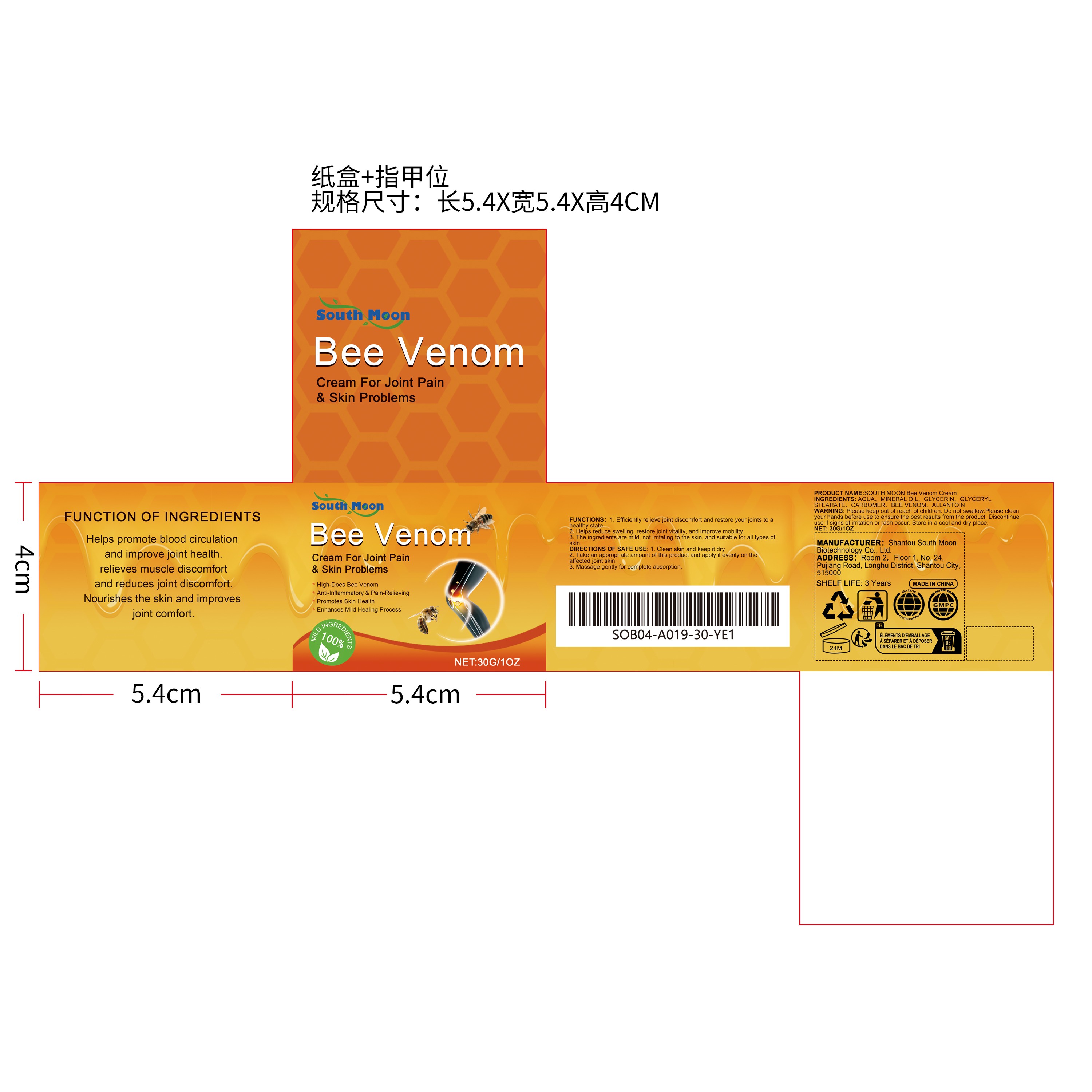 DRUG LABEL: SOUTH MOON Bee Venom Cream
NDC: 84983-006 | Form: CREAM
Manufacturer: Shantou South Moon Biotechnology Co., Ltd.
Category: otc | Type: HUMAN OTC DRUG LABEL
Date: 20251127

ACTIVE INGREDIENTS: APIS MELLIFERA VENOM 0.006 mg/30 mg
INACTIVE INGREDIENTS: GLYCERIN 0.9 mg/30 mg; MINERAL OIL 3 mg/30 mg; CARBOMER 0.06 mg/30 mg; ALLANTOIN 0.006 mg/30 mg; GLYCERYL STEARATE 0.6 mg/30 mg; AQUA 25.428 mg/30 mg

ACTIVE INGREDIENT

BEE VENOM

WHEN USING

1. Clean skin and keep it dry

2. Take an appropriate amount of this product and apply it evenly on the affected joint skin.

3. Massage gently for complete absorption.

PURPOSE

1. Efficiently relieve joint discomfort and restore your joints to a healthy state.

2. Helps reduce swelling, restore joint vitality, and improve mobility.

3. The ingredients are mild, not irritating to the skin, and suitable for all types of skin.

DO NOT USE

Discontinue use if signs of irritation or rash occur.

STOP USE

Discontinue use if signs of irritation or rash occur.

KEEP OUT OF REACH OF CHILDREN

Please keep out of reach of children. Do not swallow.

WARNINGS

Please keep out of reach of children. Do not swallow.Please clean your hands before use to ensure the best results from the product. Discontinue use if signs of irritation or rash occur. Store in a cool and dry place.

STORAGE AND HANDLING

Store in a cool and dry place.

INACTIVE INGREDIENT

AQUA
MINERAL OIL
GLYCERIN
GLYCERYL STEARATE
CARBOMER
ALLANTOIN